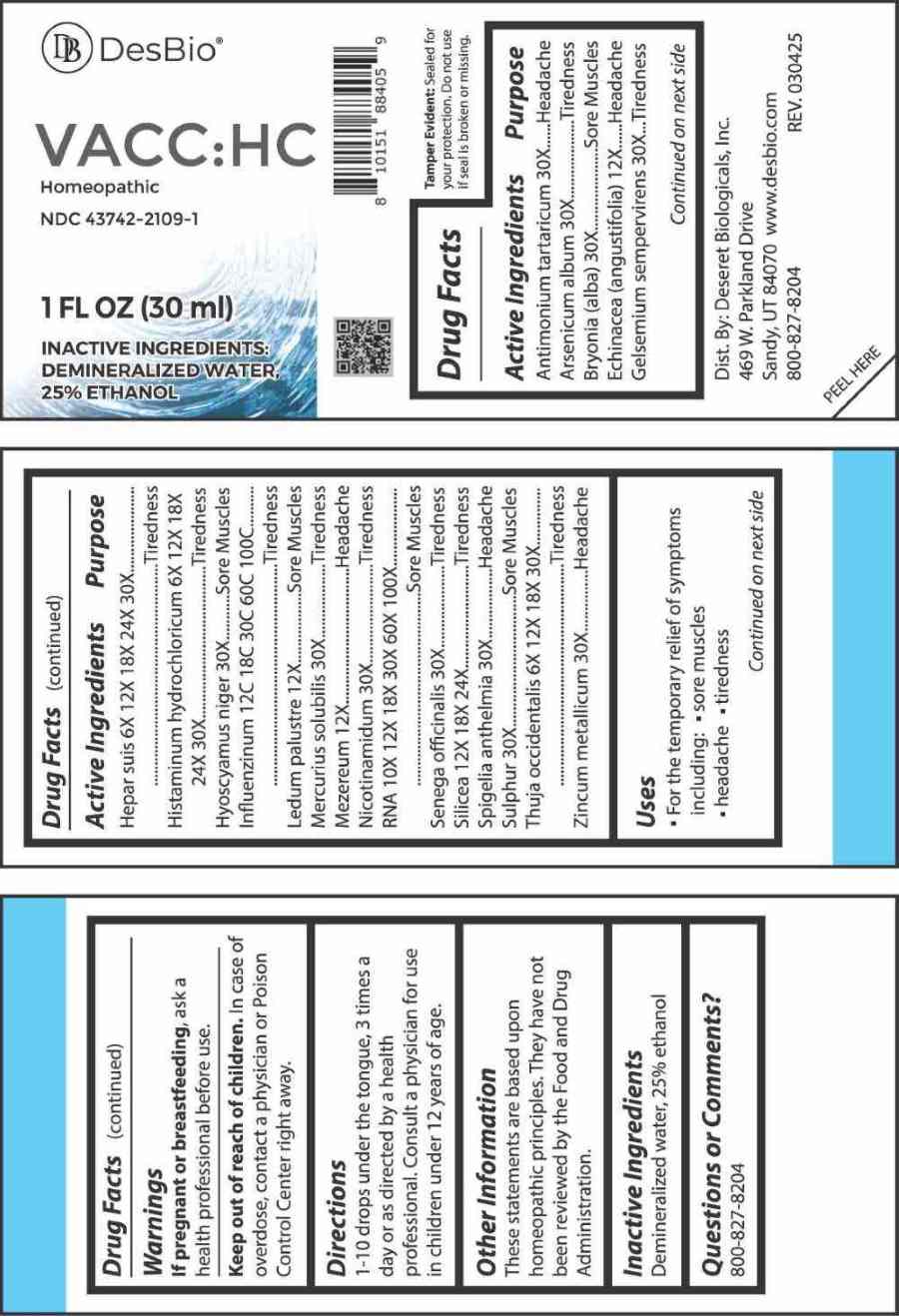 DRUG LABEL: VACC HC
NDC: 43742-2109 | Form: LIQUID
Manufacturer: Deseret Biologicals, Inc.
Category: homeopathic | Type: HUMAN OTC DRUG LABEL
Date: 20260105

ACTIVE INGREDIENTS: ANTIMONY POTASSIUM TARTRATE 30 [hp_X]/1 mL; ARSENIC TRIOXIDE 30 [hp_X]/1 mL; BRYONIA ALBA ROOT 30 [hp_X]/1 mL; ECHINACEA ANGUSTIFOLIA WHOLE 12 [hp_X]/1 mL; GELSEMIUM SEMPERVIRENS ROOT 30 [hp_X]/1 mL; PORK LIVER 6 [hp_X]/1 mL; HISTAMINE DIHYDROCHLORIDE 6 [hp_X]/1 mL; HYOSCYAMUS NIGER 30 [hp_X]/1 mL; INFLUENZA A VIRUS A/VICTORIA/4897/2022 IVR-238 (H1N1) ANTIGEN (FORMALDEHYDE INACTIVATED) 12 [hp_C]/1 mL; INFLUENZA A VIRUS A/THAILAND/8/2022 IVR-237 (H3N2) ANTIGEN (FORMALDEHYDE INACTIVATED) 12 [hp_C]/1 mL; INFLUENZA B VIRUS B/AUSTRIA/1359417/2021 BVR-26 WHOLE 12 [hp_C]/1 mL; INFLUENZA B VIRUS B/PHUKET/3073/2013 BVR-1B WHOLE 12 [hp_C]/1 mL; RHODODENDRON TOMENTOSUM LEAFY TWIG 12 [hp_X]/1 mL; MERCURIUS SOLUBILIS 30 [hp_X]/1 mL; DAPHNE MEZEREUM BARK 12 [hp_X]/1 mL; NIACINAMIDE 30 [hp_X]/1 mL; SACCHAROMYCES CEREVISIAE RNA 10 [hp_X]/1 mL; POLYGALA SENEGA ROOT 30 [hp_X]/1 mL; SILICON DIOXIDE 12 [hp_X]/1 mL; SPIGELIA ANTHELMIA WHOLE 30 [hp_X]/1 mL; SULFUR 30 [hp_X]/1 mL; THUJA OCCIDENTALIS LEAFY TWIG 6 [hp_X]/1 mL; ZINC 30 [hp_X]/1 mL
INACTIVE INGREDIENTS: WATER; ALCOHOL

DRUG FACTS:

ACTIVE INGREDIENTS:

Antimonium Tartaricum 30X, Arsenicum Album 30X, Bryonia (Alba) 30X, Echinacea (Angustifolia) 12X, Gelsemium Sempervirens 30X, Hepar Suis 6X, 12X, 18X, 24X, 30X, Histaminum Hydrochloricum 6X, 12X, 18X, 24X, 30X, Hyoscyamus Niger 30X, Influenzinum 12C, 18C, 30C, 60C, 100C, Ledum Palustre 12X, Mercurius Solubilis 30X, Mezereum 12X, Nicotinamidum 30X, RNA 10X, 12X, 18X, 30X, 60X, 100X, Senega Officinalis 30X, Silicea 12X, 18X, 24X, Spigelia Anthelmia 30X, Sulphur 30X, Thuja Occidentalis 6X, 12X, 18X, 30X, Zincum Metallicum 30X.

PURPOSE:

Antimonium Tartaricum - Headache, Arsenicum Album - Tiredness, Bryonia (Alba) – Sore Muscles, Echinacea (Angustifolia) - Headache, Gelsemium Sempervirens - Tiredness, Hepar Suis - Tiredness, Histaminum Hydrochloricum - Tiredness, Hyoscyamus Niger – Sore Muscles, Influenzinum - Tiredness, Ledum Palustre – Sore Muscles, Mercurius Solubilis - Tiredness, Mezereum - Headache, Nicotinamidum - Tiredness, RNA – Sore Muscles, Senega Officinalis - Tiredness, Silicea - Tiredness, Spigelia Anthelmia - Headache, Sulphur – Sore Muscles, Thuja Occidentalis - Tiredness, Zincum Metallicum - Headache

USES:

• For the temporary relief of symptoms including:

• sore muscles • headache • tiredness

These statements are based upon homeopathic principles. They have not been reviewed by the Food and Drug Administration.

WARNINGS:

If pregnant or breastfeeding, ask a health professional before use.

Keep out of reach of children. In case of overdose, contact a physician or Poison Control Center right away.

Tamper Evident: Sealed for your protection. Do not use if seal is broken or missing.

KEEP OUT OF REACH OF CHILDREN:

In case of overdose, contact physician or a Poison Control Center right away.

DIRECTIONS:

1-10 drops under the tongue, 3 times a day or as directed by a health professional. Consult a physician for use in children under 12 years of age.

INACTIVE INGREDIENTS:

Demineralized water, 25% ethanol

QUESTIONS:

Dist. By: Deseret Biologicals, Inc.
469 W. Parkland Drive
Sandy, UT 84070

www.desbio.com

800-827-8204

PACKAGE LABEL DISPLAY:

DesBio

VACC:HC

Homeopathic

NDC 43742-2109-1

1 FL OZ (30 ml)